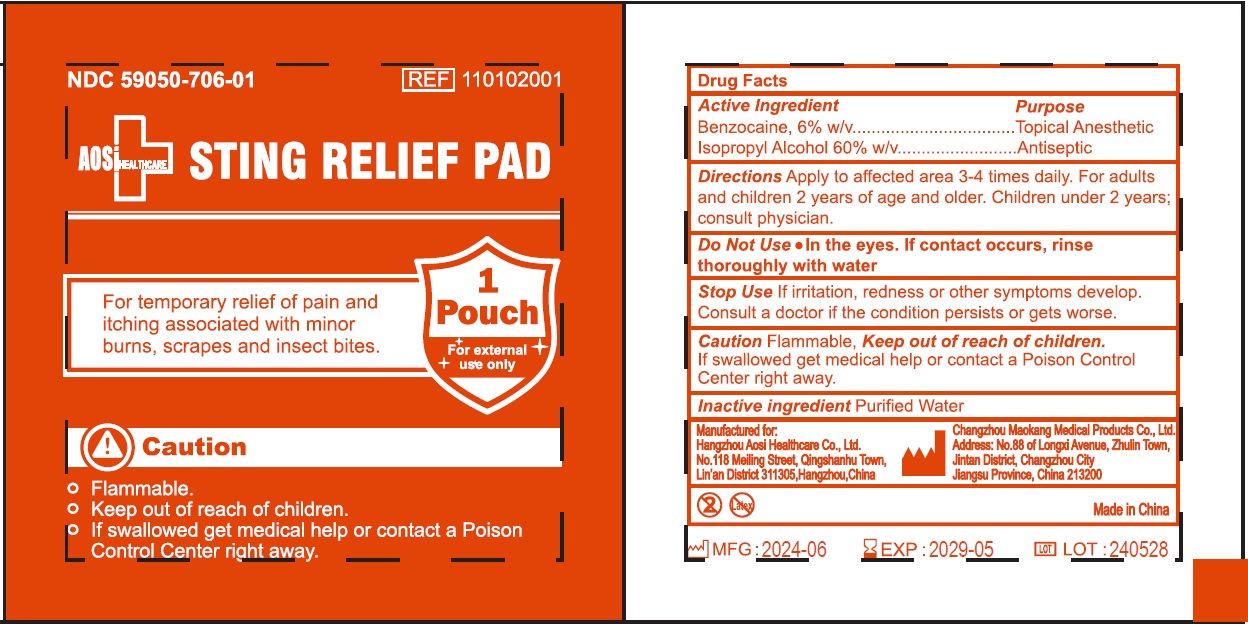 DRUG LABEL: Sting Relief Pad
NDC: 59050-706 | Form: LIQUID
Manufacturer: Changzhou Maokang Medical Products Co., Ltd
Category: otc | Type: HUMAN OTC DRUG LABEL
Date: 20241121

ACTIVE INGREDIENTS: BENZOCAINE 60 mg/1 g; ISOPROPYL ALCOHOL 0.6 mL/1 g
INACTIVE INGREDIENTS: WATER

Sting Relief Pad

Active Ingredient

Benzocaine, 6% w/v

Isopropyl Alcohol 60% w/v

Purpose

Topical Anesthetic

Antiseptic

Directions

Apply to affected area 3-4 times daily.

DOSAGE AND ADMINISTRATION

For adults and children 2 years of age and older. Children under 2 years; consult physician.

WARNINGS

Do Not Use

- In the eyes. If contact occurs, rinse thoroughly with water

Stop Use

If irritation, redness or other symptoms develop. Consult a doctor if the condition persists or gets worse.

CautionFlammable , Keep out of reach of children.

If swallowed get medical help or contact a Poison Control Center right away.

Inactive ingredient

Purified Water